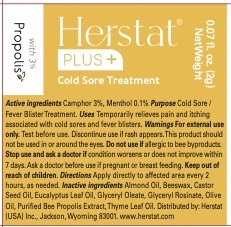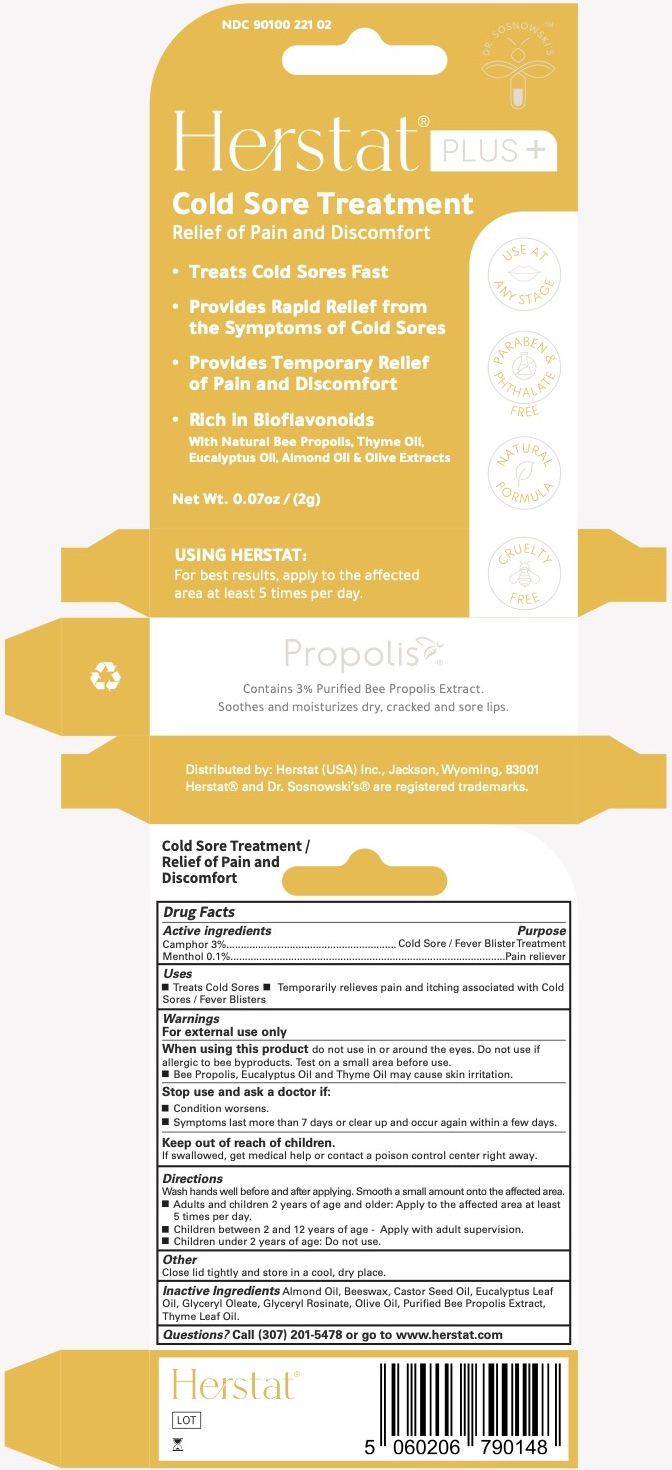 DRUG LABEL: HERSTAT PLUS Cold Sore Treatment
NDC: 90100-221 | Form: OINTMENT
Manufacturer: Herstat (USA) Inc.
Category: otc | Type: HUMAN OTC DRUG LABEL
Date: 20250118

ACTIVE INGREDIENTS: CAMPHOR (SYNTHETIC) 3 g/100 g; MENTHOL 0.1 g/100 g
INACTIVE INGREDIENTS: CASTOR OIL; YELLOW WAX; EUCALYPTUS OIL; ALMOND OIL; PROPOLIS WAX; THYME OIL; GLYCERYL OLEATE; GLYCERYL ROSINATE; OLIVE OIL

HERSTAT PLUS Cold Sore Treatment
Moisturizing Lip Care Stick

ACTIVE INGREDIENTS

Camphor 3%

Menthol 0.1%

PURPOSE

Cold Sore / Fever BlisterTreatment

Pain reliever

USES

Treats Cold Sores Temporarily relieves pain and itching associated with Cold Sores / Fever Blisters

WARNINGS

For external use only.

When using this product do not use in or around the eyes. Do not use if allergic to bee byproducts. Test on a small area before use.

- Bee Propolis, Eucalyptus Oil and Thyme Oil may cause skin irritation.

Stop use and ask a doctor if:

• Condition worsens.
• Symptoms last more than 7 days or clear up and occur again within a few days.

Keep out of reach of children.

If swallowed, get medical help or contact a poison control center right away.

DIRECTIONS

Wash hands well before and after applying. Smooth a small amount onto the affected area. Adults and children 2 years of age and older: Apply to the affected area at least 5 times per day.

Children between 2 and 12 years of age - Apply with adult supervision. Children under 2 years of age: Do not use.

OTHER

Close cap tightly and store in a cool, dry place.

INACTIVE INGREDIENTS

Almond Oil, Beeswax, Castor Seed Oil, Eucalyptus Leaf Oil, Glyceryl Oleate, Glyceryl Rosinate, Olive Oil, Purified Bee Propolis Extract, Thyme Leaf Oil.

QUESTIONS?

Questions? Call (307) 201-5478 or go to www.herstat.com

Herstat Cold Sore Treatment

Herstat®

Herstat Cold Sore Treatment

0.7 OZ (2g) Net Weight